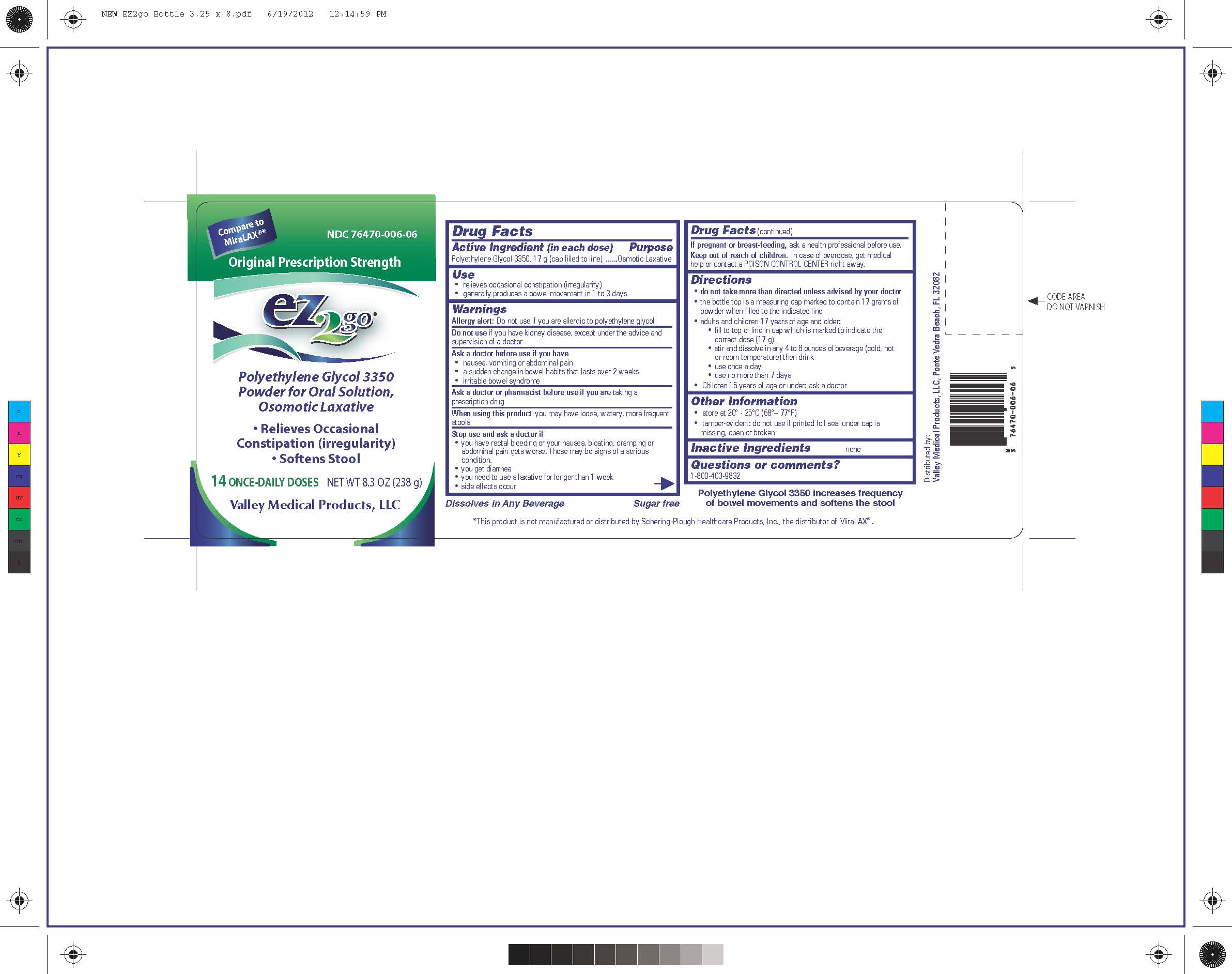 DRUG LABEL: EZ2go
NDC: 76470-006 | Form: POWDER
Manufacturer: Valley Medical Products,LLC
Category: otc | Type: HUMAN OTC DRUG LABEL
Date: 20200911

ACTIVE INGREDIENTS: POLYETHYLENE GLYCOL 3350 17 g/17 g

Drug Facts

Inactive Ingredients none

Active Ingredient (in each dose)

Polyethylene Glycol 3350, 17 g (cap filled to line)

Purpose

Osmotic Laxative

Warnings

Allergy Alert: Do not use if you are allergic to polyethylene glycol

Do not use if you have kidney disease, except under the advice and supervision of a doctor

When using this product, you may have loose, watery, more frequent bowel movements

Ask a doctor before use if you have

-nausea, vomiting or abdominal pain

-a sudden change in bowel habits that lasts over 2 weeks

-irritable bowel syndrome

Ask a doctor or pharmacist before use if you are taking a prescription drug

Stop use and ask a doctor if

- you have rectal bleeding or your nausea, bloating, cramping or abdominal pain gets worse.These may be sogns of a serious condition.

- you get diarrhea

- you need to use a laxative for longer than 1 week

- side effects occur

Keep out of reach of children. In case of overdose, get medical help or contact a POISON CONTROL CENTER right away.

PREGNANCY OR BREAST FEEDING

If pregnant or breast-feeding, ask a health professional before use.

Directions

-do not take more than directed unless advised by your doctor

-the bottle top is a measuring cap marked to contain 17 grams of powder when filled to the indicated line

-adults and children 17 years of age and older:

-fill to top of line in cap which is marked to indicate the correct dose (17 g)

-stir and dissolve in any 4 to 8 ounces of beverage (cold, hot or room temperature) and then drink

-use once a day

-use no more than 7 days

-Children 16 years of age or under: ask a doctor

Questions or comments?

1-800-403-9832

Use

-relieves occasional constipation (irregularity)

-generally produces a bowel movement in 1 to 3 days